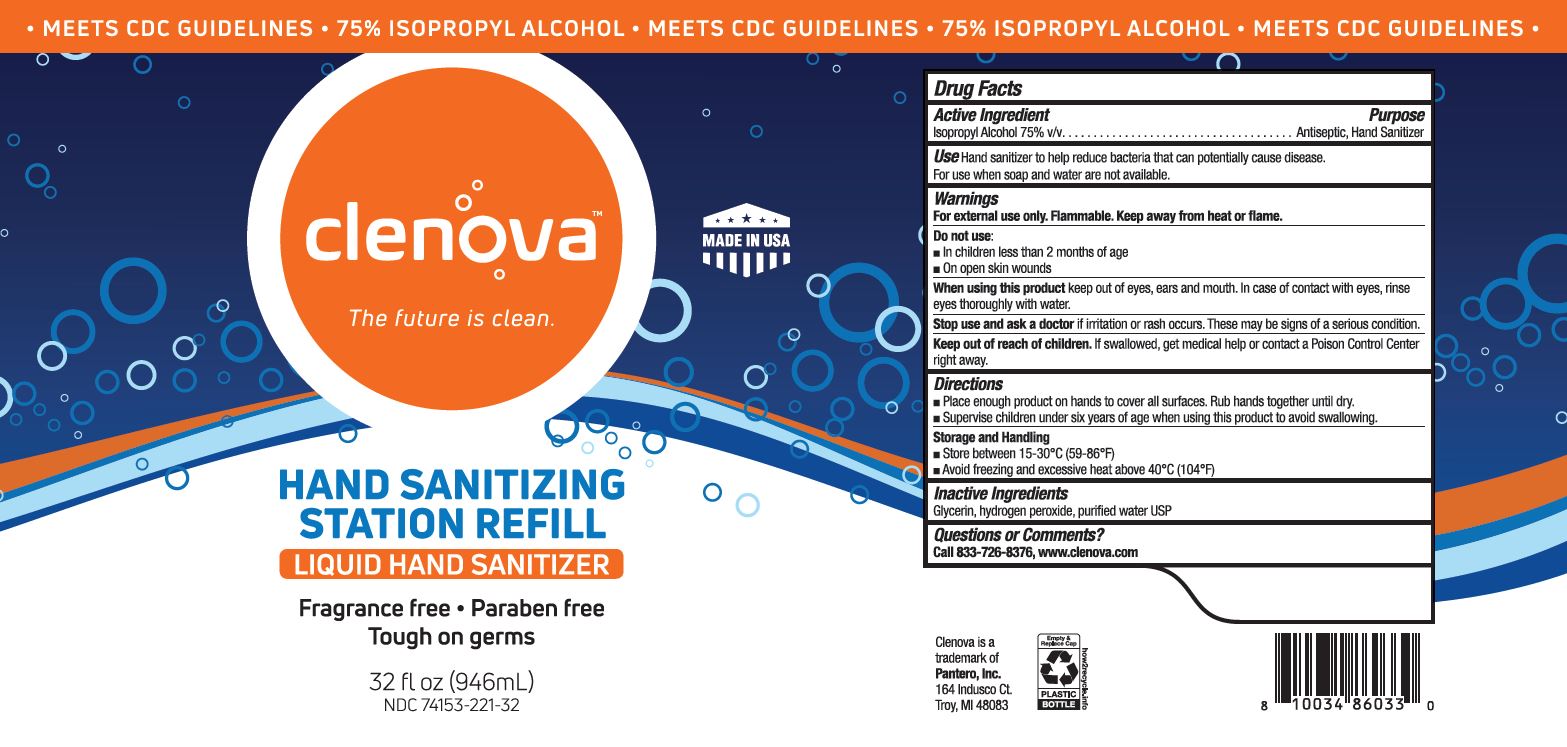 DRUG LABEL: Clenova Hand Sanitizer 75% ISA
NDC: 74153-221 | Form: LIQUID
Manufacturer: Pantero
Category: otc | Type: HUMAN OTC DRUG LABEL
Date: 20200925

ACTIVE INGREDIENTS: ISOPROPYL ALCOHOL 75 mL/100 mL
INACTIVE INGREDIENTS: GLYCERIN; HYDROGEN PEROXIDE; WATER

Clenova Hand Sanitizer 75% IPA

Active Ingredient(s)

Isopropyl Alcohol 75% v/v

Purpose

Antiseptic, Hand Sanitizer

Use

Hand Sanitizer to help reduce bacteria that can potentially cause disease. For use when soap and water are not available.

Warnings

For external use only. Flammable. Keep away from heat or flame

Do not use

- in children less than 2 months of age
- on open skin wounds

When using this product keep out of eyes, ears and mouth. In case of contact with eyes, rinse eyes thoroughly with water.

Stop use and ask a doctor if irritation or rash occurs. These may be signs of a serious condition.

Keep out of reach of children. If swallowed, get medical help or contact a Poison Control Center right away.

Directions

- Place enough product on hands to cover all surfaces. Rub hands together until dry.
- Supervise children under six years of age when using this product to avoid swallowing.

Other information

- Store between 15-30C (59-86F)
- Avoid freezing and excessive heat above 40C (104F)

Inactive ingredients

Glycerin, hydrogen peroxide, purified water USP

Questions or Comments?

Call 833-726-8376, www.clenova.com

Package Label - Principal Display Panel

946 ml NDC: 74153-221-32